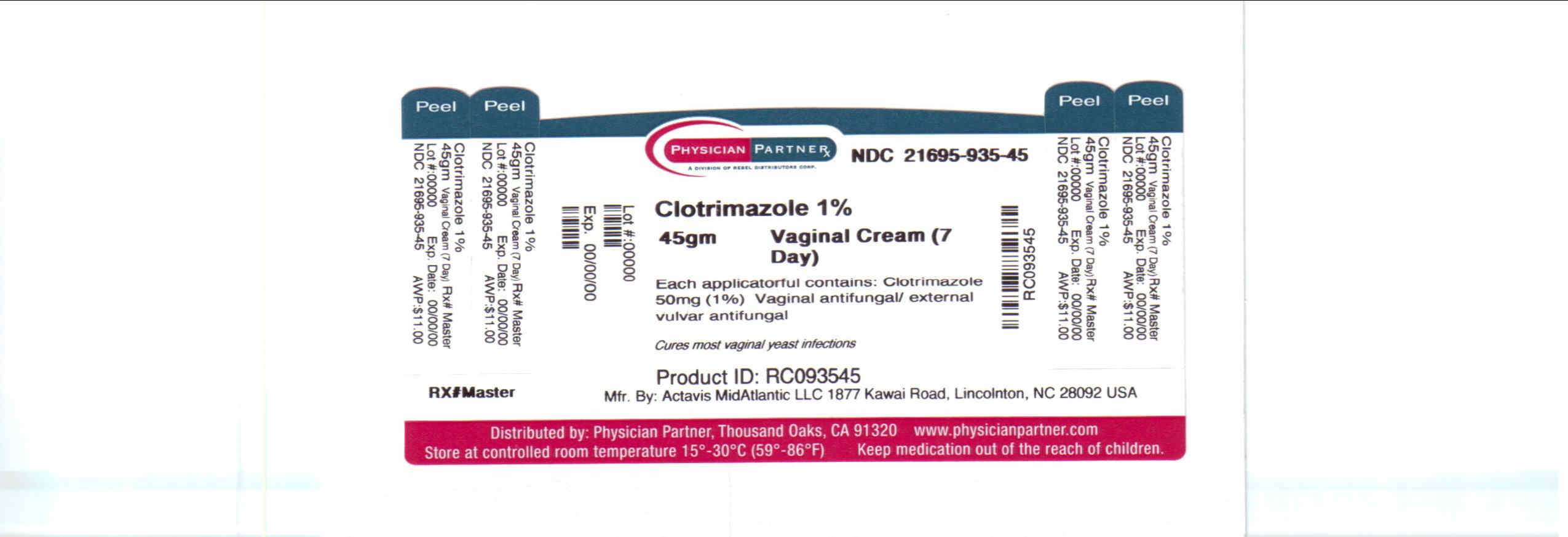 DRUG LABEL: Clotrimazole
NDC: 21695-935 | Form: CREAM
Manufacturer: Rebel Distributors Corp.
Category: otc | Type: HUMAN OTC DRUG LABEL
Date: 20110511

ACTIVE INGREDIENTS: CLOTRIMAZOLE 50 mg/1 g
INACTIVE INGREDIENTS: BENZYL ALCOHOL; CETOSTEARYL ALCOHOL; CETYL ESTERS WAX; OCTYLDODECYL STEARATE; POLYSORBATE 60; WATER; SODIUM PHOSPHATE, MONOBASIC, MONOHYDRATE; SORBITAN MONOSTEARATE

Clotrimazole Drug Facts

Active ingredient

Clotrimazole 50mg

Purpose

Vaginal antifungal/external vulvar antifungal

Keep Out of Reach of Children

If swallowed, get medical help or contact a Poison Control Center right away.

Uses

Treats vaginal yeast (candida) infections

Relieves external vulvar itching and irritation associated with a yeast infection

Warnings

For vaginal or external vulvar use only.

Do not use:

° If you have abdominal pain, fever, or a foul smelling vaginal discharge.

Contact your doctor immediately.

° In children less than 12 years of age.

Ask a doctor before use if you have:

° vaginal or vulvar itching and discomfort for the first time. If you have had a doctor diagnose a vaginal yeast infection before and have the same symptoms now, use this cream as directed for 7 days in a row.

° symptoms that return within 2 months or infections that do not clear up easily with proper treatment. You could be pregnant, or there could be a serious underlying medical cause for your infections, including diabetes or a damaged immune system (including damage from infection from HIV - the virus that causes AIDS). Please read enclosed educational pamphlet.

When using this product do not use tampons.

Stop use and ask a doctor if:

symptoms do not get better in 3 days or infection isn't gone in 7 days. You may have a condition other than a yeast infection.

If pregnant or breast-feeding, ask a health professional before use.

Directions

° before using this product, read the enclosed pamphlet

° fill the applicator and insert one applicatorful of cream into the vagina, preferably at bedtime. Repeat this procedure 7 days in a row. Throw applicator away after use.

° for relief of external vulvar itching, squeeze a small amount of cream onto your finger and gently spread the cream onto the irritated area of the vulva. Use once or twice a day for up to 7 days as needed to relieve external vulvar itching. The cream should not be used for vulvar itching due to causes other than a yeast infection.

Other Information

° store at room temperature between 2° and 30°C (36° to 86°F)°

° see end flaps of carton and tube for lot number and expiration date

° safety sealed: the tube opening should be sealed. If seal has been punctured or is not visible, do not use the product.

Questions? 1-800-432-8534 (select option #2) between 9 am and 4 pm EST, Monday-Friday.

Inactive ingredients

benzyl alcohol, cetostearyl alcohol, cetyl esters wax, 2-octyldodecanol, polysorbate 60, purified water, sodium phosphate monobasic, sorbitan monostearate.